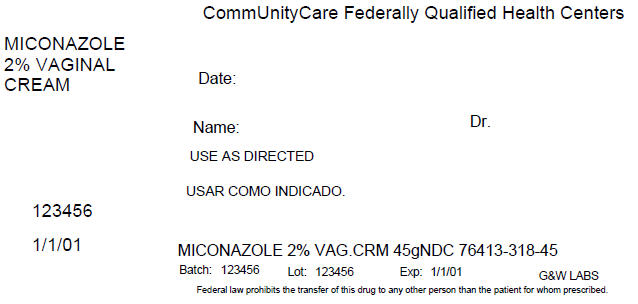 DRUG LABEL: Miconazole Nitrate 
NDC: 76413-318 | Form: CREAM
Manufacturer: Central Texas Community Health Centers
Category: otc | Type: HUMAN OTC DRUG LABEL
Date: 20160421

ACTIVE INGREDIENTS: Miconazole Nitrate 20 mg/1 g
INACTIVE INGREDIENTS: Benzoic Acid; Butylated Hydroxyanisole; Mineral Oil; Peg-5 Oleate; Pegoxol 7 Stearate; Water

Miconazole nitrate

ACTIVE INGREDIENT

Miconazole nitrate 2% (100 mg in each applicator)
Miconazole nitrate 2% (as external cream)

PURPOSE

Vaginal antifungal

USES

• treats repeat vaginal yeast infections
• relieves external itching and irritation due to a repeat vaginal yeast infection

WARNINGS

For vaginal use only
Do not use if you have never had a vaginal yeast infection diagnosed by a doctor
Ask a doctor before use if you have
• vaginal itching and discomfort for the first time
• lower abdominal, back or shoulder pain, fever, chills, nausea, vomiting, or foul-smelling vaginal discharge. You may have a more serious condition.
• vaginal yeast infections often (such as once a month or 3 in 6 months). You could be pregnant or have a serious underlying medical cause for your symptoms, including diabetes or a weakened immune system.
• been exposed to the human immunodeficiency virus (HIV) that causes AIDS.
Ask a doctor or pharmacist before use if you are taking the prescription blood thinning medication warfarin, because bleeding or bruising may occur.
When using this product
• do not use tampons, douches, spermicides, or other vaginal products
• do not have vaginal intercourse
• condoms and diaphragms may be damaged and fail to prevent pregnancy or sexually transmitted diseases (STDs)
Stop use and ask a doctor if
• symptoms do not get better in 3 days
• symptoms last more than 7 days
• you get a rash or hives, abdominal pain, fever, chills, nausea, vomiting,or foul-smelling vaginal discharge

IF PREGNANT OR BREAST FEEDING,

ask a health professional before use.

KEEP OUT OF REACH OF CHILDREN

If swallowed, get medical help or contact a Poison Control Center right away.

DOSAGE & ADMINISTRATION

• before using this product read the enclosed consumer information leaflet for complete instructions
• adults and children 12 years of age and over:
• applicator: insert one applicatorful into the vagina at bedtime for 7 nights in a row
• external cream: squeeze a small amount of cream onto your fingertip. Gently apply the cream onto the itchy, irritated
skin outside the vagina. Use daily for up to 7 days as needed
• children under 12 years of age: ask a doctor

OTHER INFORMATION

• do not use if seal over tube opening has been punctured or cannot be seen
• store at room temperature 15°-30°C (59°-86°F). Avoid heat over 30°C or 86°F.

INACTIVE INGREDIENT

benzoic acid, BHA, mineral oil, peglicol 5 oleate, pegoxol 7 stearate, purified water

PRINCIPAL DISPLAY PANEL - 45 g Tube Label

CommUnityCare Federally Qualified Health Centers

MICONAZOLE
2% VAGINAL
CREAM

Date:

Name:
Dr.

USE AS DIRECTED

123456

1/1/01

MICONAZOLE 2% VAG.CRM 45gNDC 76413-318-45

Batch: 123456
Lot: 123456
Exp: 1/1/01
G&W LABS

Federal law prohibits the transfer of this drug to any other person than the patient for whom prescribed.